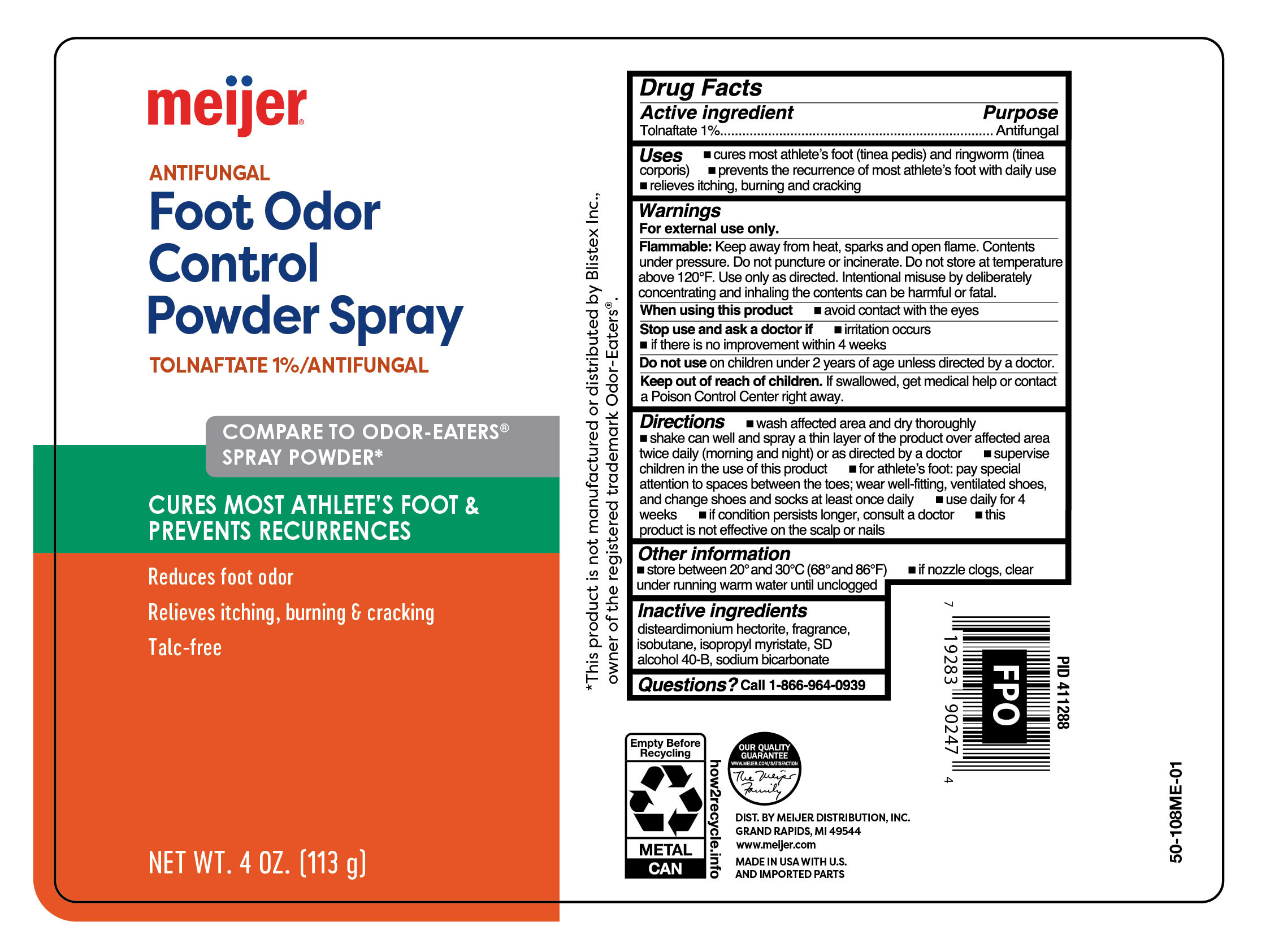 DRUG LABEL: Foot Odor Control Powder
NDC: 79481-0622 | Form: AEROSOL, SPRAY
Manufacturer: Meijer Distribution Inc
Category: otc | Type: HUMAN OTC DRUG LABEL
Date: 20251212

ACTIVE INGREDIENTS: TOLNAFTATE 10 mg/1 g
INACTIVE INGREDIENTS: DISTEARDIMONIUM HECTORITE; ISOBUTANE; ALCOHOL; SODIUM BICARBONATE

Meijer Foot Odor Control Powder Spray

Active ingredient

Tolnaftate 1%

Purpose

Antifungal

Uses

- cures mose athlete's foot (tinea pedis) and ringworm (tinea corporis)
- prevents recurrence of athlete's foot with daily use
- relieves itching, burning and cracking

Warnings

For external use only.

Flammable:

Keep away from heat, sparks and open flame. Contents under pressure. Do not puncture or incinerate. Do not store at temperature above 120°F. Use only as directed. Intentional misuse by deliberately concentrating and inhaling the contents can be harmful or fatal.

When using this product

- avoid contact with the eyes

Stop use and ask a doctor if

- irritation occurs
- if there is no improvement within 4 weeks

Do not use

on children under 2 years of age unless directed by a doctor.

Keep out of reach of children.

If swallowed, get medical help or contact a Poison Control Center right away.

Directions

- wash affected area and dry thoroughly
- shake can well and spray a thin layer over affected area twice daily (morning and night) or as directed by a doctor
- supervise children in the use of this product
- for athlete's foot: pay special attention to spaces between the toes; wear well-fitting, ventilated shoes, and change shoes and socks at least once daily
- use daily for 4 weeks
- if conditions persists, consult a doctor
- this product is not effective on the scalp or nails

Other information

- store between 20º and 30ºC (68º and 86ºF)
- if nozzle clogs, clear under running warm water until clogged

Inactive ingredients

disteardimonium hectorite, fragrance, isobutane, isopropyl myristate, SD alcohol 40-B, sodium bicarbonate

Questions?

call 1-866-964-0939

RECENT MAJOR CHANGES

.

Principal Display Panel

meijer

ANTIFUNAL

Foot Odor

Control

Powder Spray

TOLNAFTATE 1%/ANTIFUNGAL

CURES MOST ATHLETE'S FOOT

& PREVENTS RECURRENCES

Reduces foot odor

Relieves itching,burning & cracking

Talc-free

NET WT. 4 OZ. (113g)